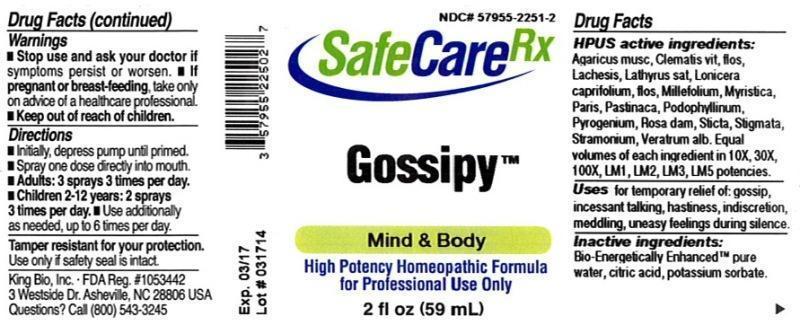 DRUG LABEL: Gossipy
NDC: 57955-2251 | Form: LIQUID
Manufacturer: King Bio Inc.
Category: homeopathic | Type: HUMAN OTC DRUG LABEL
Date: 20140331

ACTIVE INGREDIENTS: AMANITA MUSCARIA FRUITING BODY 10 [hp_X]/59 mL; CLEMATIS VITALBA FLOWER 10 [hp_X]/59 mL; LACHESIS MUTA VENOM 10 [hp_X]/59 mL; LATHYRUS SATIVAS SEED 10 [hp_X]/59 mL; LONICERA CAPRIFOLIUM FLOWERING TOP 10 [hp_X]/59 mL; ACHILLEA MILLEFOLIUM 10 [hp_X]/59 mL; VIROLA SEBIFERA RESIN 10 [hp_X]/59 mL; PARIS QUADRIFOLIA 10 [hp_X]/59 mL; PARSNIP 10 [hp_X]/59 mL; PODOPHYLLUM RESIN 10 [hp_X]/59 mL; RANCID BEEF 10 [hp_X]/59 mL; ROSA DAMASCENA FLOWERING TOP 10 [hp_X]/59 mL; LOBARIA PULMONARIA 10 [hp_X]/59 mL; CORN SILK 10 [hp_X]/59 mL; DATURA STRAMONIUM 10 [hp_X]/59 mL; VERATRUM ALBUM ROOT 10 [hp_X]/59 mL
INACTIVE INGREDIENTS: WATER; CITRIC ACID MONOHYDRATE; POTASSIUM SORBATE

Gossipy

ACTIVE INGREDIENT

HPUS active ingredients: Agaricus muscarius, Clematis vitalba, flos, Lachesis mutus, Lathyrus sativus, Lonicera caprifolium, flos, Millefolium, Myristica sebifera, Paris quadrifolia, Pastinaca sativa, Podophyllinum, Pyrogenium, Rosa damascena, Sticta pulmonaria, Stigmata maidis, Stramonium, Veratrum album. Equal volumes of each ingredient in 10X, 30X, 100X, LM1, LM2, LM3, LM5 potencies.

PURPOSE

Uses for temporary relief of: gossip, incessant talking, hastiness, indiscretion, meddling, uneasy feeling during silence.

Inactive Ingredients:

Bio-Energetically Enhanced™ pure water base, Citric acid and Potassium sorbate.

Warning

- Stop use and ask a doctor. If symptoms persist or worsen.
- If pregnant or breast-feeding, ask a healthcare professional before use.

- Keep out of reach of children.

Directions

- Initially, depress pump until primed.
- Spray one dose directly into mouth.
- Adults: 3 sprays 3 times per day.
- Children: 2-12 years: 2 sprays 3 times per day.
- Use additonally as needed, up to 6 times per day.

Other Information

Tamper resistant for your protection. Use only if safety seal is intact.

INDICATIONS AND USAGE

Uses for temporary relief of:

- gossip
- incessant talking
- hastiness
- indiscretion
- meddling
- uneasy feeling during silence